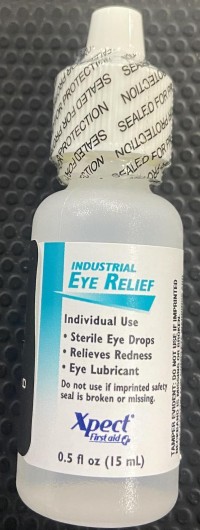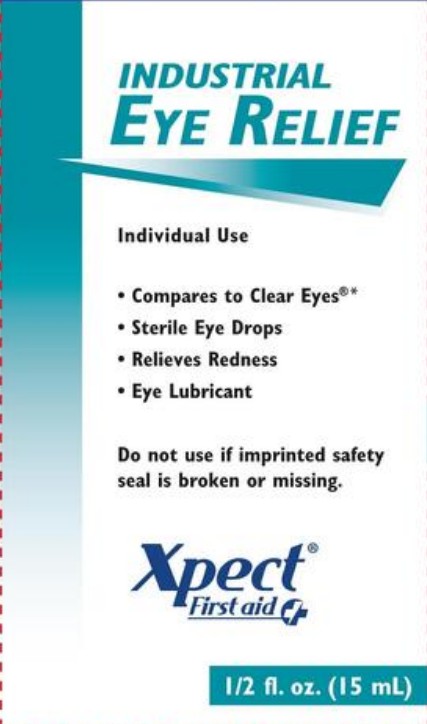 DRUG LABEL: Xpect Industrial Eye Relief
NDC: 42961-255 | Form: SOLUTION/ DROPS
Manufacturer: Cintas Corporation
Category: otc | Type: HUMAN OTC DRUG LABEL
Date: 20250930

ACTIVE INGREDIENTS: NAPHAZOLINE HYDROCHLORIDE 0.012 g/100 mL; GLYCERIN 0.25 g/100 mL
INACTIVE INGREDIENTS: BORIC ACID; EDETATE DISODIUM; SODIUM BORATE; BENZALKONIUM CHLORIDE; WATER

Xpect Industrial Eye Relief 15mL (PLD)

Active ingredients

Glycerin 0.25%

Naphazoline HCl 0.012%

Purposes

Lubricant

Redness reliever

Uses

- relieves redness of the eye due to minor eye irritations
- for use as a protectant against further irritation or to relieve dryness of the eye
- for the temporary relief of burning and irritation due to dryness of the eye

Warnings

For external use only

Do not use

if solution changes color or becomes cloudy

Ask a doctor before use if you have

narrow angle glaucoma

When using this product

- to avoid contamination, do not touch tip of container to any surface
- replace cap after using
- overuse may produce increased redness of the eye
- pupils may become enlarged temporarily

Stop use and ask a doctor if

- you experience eye pain
- you experience changes in vision
- you experience continued redness or irritation of the eye
- the condition worsens or persists for more than 72 hours

Keep out of reach of children.

If swallowed, get medical help or contact a Poison Control Center (1-800-222-1222) right away.

Directions

instill 1 to 2 drops in the affected eye(s) up to 4 times daily

Other information

store at room temperature

Inactive ingredients

benzalkonium chloride, boric acid, edetate disodium, purified water, sodium borate

Questions?

1-877-973-2811

Monday-Friday

8:00am-5:00pm

Xpect Industrial Eye Relief 15mL

INDUSTRIAL EYE RELIEF

Individual Use

- Compares to Clear Eyes®*
- Sterile Eye Drops
- Relieve Redness
- Eye Lubricant

Do not use if imprinted safety seal is broken or missing.

Xpect® First aid

1/2 fl. oz. (15 mL)

INDUSTRIAL EYE RELIEF

Individual Use

- Sterile Eye Drops
- Relieve Redness
- Eye Lubricant

Do not use if imprinted safety seal is broken or missing.

Xpect® First aid

0.5 fl. oz. (15 mL)